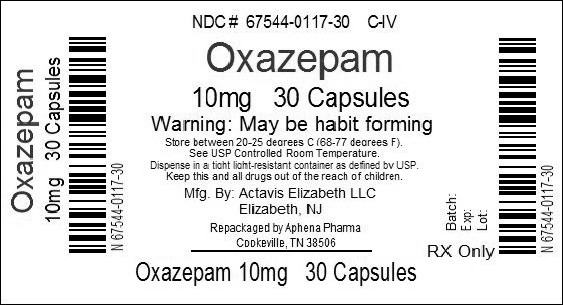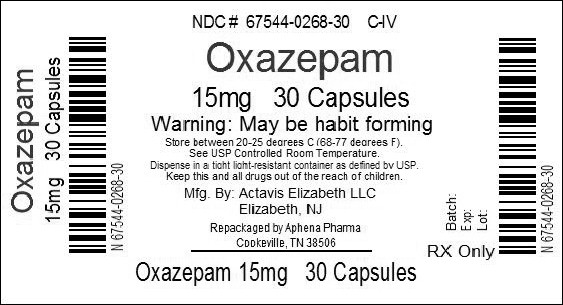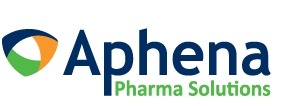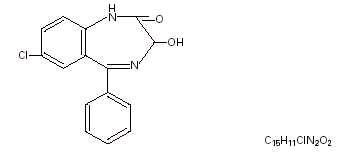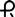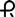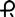 DRUG LABEL: Oxazepam
NDC: 67544-117 | Form: CAPSULE, GELATIN COATED
Manufacturer: Aphena Pharma Solutions - Tennessee, LLC
Category: prescription | Type: HUMAN PRESCRIPTION DRUG LABEL
Date: 20191220
DEA Schedule: CIV

ACTIVE INGREDIENTS: OXAZEPAM 10 mg/1 1
INACTIVE INGREDIENTS: STARCH, CORN; CROSCARMELLOSE SODIUM; FD&C RED NO. 40; GELATIN, UNSPECIFIED; HYPROMELLOSE, UNSPECIFIED; LACTOSE MONOHYDRATE; MAGNESIUM STEARATE; METHYLPARABEN; PROPYLPARABEN; SODIUM LAURYL SULFATE; TITANIUM DIOXIDE; D&C RED NO. 28

OXAZEPAM CAPSULES, USP

CIV

40-9188

Revised — March 2012

Rx only

DESCRIPTION

Oxazepam is the first of a chemical series of compounds known as the 3-hydroxybenzodiazepinones. A therapeutic agent providing versatility and flexibility in control of common emotional disturbances, this product exerts prompt action in a wide variety of disorders associated with anxiety, tension, agitation, and irritability, and anxiety associated with depression. In tolerance and toxicity studies on several animal species, this product reveals significantly greater safety factors than related compounds (chlordiazepoxide and diazepam) and manifests a wide separation of effective doses and doses inducing side effects.

Oxazepam capsules contain 10 mg, 15 mg or 30 mg oxazepam. The following inactive ingredients are contained in these capsules: corn starch, croscarmellose sodium, FD&C Red #40, gelatin, hypromellose, lactose (monohydrate), magnesium stearate, methylparaben, propylparaben, sodium lauryl sulfate, titanium dioxide, and other inert ingredients. The 10 mg capsule also contains D&C Red #28. The 15 mg capsule also contains D&C Yellow #10. The 30 mg capsule also contains D&C Red #28 and FD&C Blue #1.

Oxazepam is 7-chloro-1,3-dihydro-3-hydroxy-5-phenyl-2H-1,4-benzodiazepin-2-one. A white crystalline powder with a molecular weight of 286.72, its structural formula is as follows:

CLINICAL PHARMACOLOGY

Pharmacokinetic testing in healthy adult subjects has demonstrated that a single 30 mg dose of a capsule or tablet will result in equivalent extent of absorption. Peak plasma levels were observed to occur about 3 hours after dosing. The mean elimination half-life for oxazepam was approximately 8.2 hours (range 5.7 to 10.9 hours).

This product has a single, major inactive metabolite in man, a glucuronide excreted in the urine.

Age (<80 years old) does not appear to have a clinically significant effect on oxazepam kinetics. A statistically significant increase in elimination half-life in the very elderly (>80 years of age) as compared to younger subjects has been reported, due to a 30% increase in volume of distribution, as well as a 50% reduction in unbound clearance of oxazepam in the very elderly. (see PRECAUTIONS, Geriatric Use).

INDICATIONS AND USAGE

Oxazepam is indicated for the management of anxiety disorders or for the short-term relief of the symptoms of anxiety. Anxiety or tension associated with the stress of everyday life usually does not require treatment with an anxiolytic.

Anxiety associated with depression is also responsive to Oxazepam therapy.

This product has been found particularly useful in the management of anxiety, tension, agitation, and irritability in older patients.

Alcoholics with acute tremulousness, inebriation, or with anxiety, associated with alcohol withdrawal are responsive to therapy.

The effectiveness of Oxazepam in long-term use, that is, more than 4 months, has not been assessed by systematic clinical studies. The physician should periodically reassess the usefulness of the drug for the individual patient.

CONTRAINDICATIONS

History of previous hypersensitivity reaction to oxazepam. Oxazepam is not indicated in psychoses.

WARNINGS

As with other CNS-acting drugs, patients should be cautioned against driving automobiles or operating dangerous machinery until it is known that they do not become drowsy or dizzy on oxazepam therapy.

Patients should be warned that the effects of alcohol or other CNS-depressant drugs may be additive to those of Oxazepam, possibly requiring adjustment of dosage or elimination of such agents.

Withdrawal symptoms of the barbiturate type have occurred after the discontinuation of benzodiazepines (see DRUG ABUSE AND DEPENDENCE section).

Use in Pregnancy:

An increased risk of congenital malformations associated with the use of minor tranquilizers (chlordiazepoxide, diazepam, and meprobamate) during the first trimester of pregnancy has been suggested in several studies. Oxazepam, a benzodiazepine derivative, has not been studied adequately to determine whether it, too, may be associated with an increased risk of fetal abnormality. Because use of these drugs is rarely a matter of urgency, their use during this period should almost always be avoided. The possibility that a woman of childbearing potential may be pregnant at the time of institution of therapy should be considered. Patients should be advised that if they become pregnant during therapy or intend to become pregnant they should communicate with their physician about the desirability of discontinuing the drug.

PRECAUTIONS

General

Although hypotension has occurred only rarely, oxazepam should be administered with caution to patients in whom a drop in blood pressure might lead to cardiac complications. This is particularly true in the elderly patient.

Information for Patients

To assure the safe and effective use of oxazepam, patients should be informed that, since benzodiazepines may produce psychological and physical dependence, it is advisable that they consult with their physician before either increasing the dose or abruptly discontinuing this drug.

Pediatric Use

Safety and effectiveness in pediatric patients under 6 years of age have not been established. Absolute dosage for pediatric patients 6 to 12 years of age is not established.

Geriatric Use

Clinical studies of oxazepam were not adequate to determine whether subjects aged 65 and over respond differently than younger subjects. Age (<80 years old) does not appear to have a clinically significant effect on oxazepam kinetics (see CLINICAL PHARMACOLOGY).

Clinical circumstances, some of which may be more common in the elderly, such as hepatic or renal impairment, should be considered. Greater sensitivity of some older individuals to the effects of oxazepam (e.g., sedation, hypotension, paradoxical excitation) cannot be ruled out (see PRECAUTIONS, General; see ADVERSE REACTIONS). In general, dose selection for oxazepam for elderly patients should be cautious, usually starting at the lower end of the dosing range (see DOSAGE AND ADMINISTRATION).

ADVERSE REACTIONS

The necessity for discontinuation of therapy due to undesirable effects has been rare. Transient, mild drowsiness is commonly seen in the first few days of therapy. If it persists, the dosage should be reduced. In few instances, dizziness, vertigo, headache, and rarely syncope have occurred either alone or together with drowsiness. Mild paradoxical reactions, i.e., excitement, stimulation of affect, have been reported in psychiatric patients; these reactions may be secondary to relief of anxiety and usually appear in the first two weeks of therapy.

Other side effects occurring during oxazepam therapy include rare instances of nausea, lethargy, edema, slurred speech, tremor, altered libido, and minor diffuse skin rashes — morbilliform, urticarial, and maculopapular. Such side effects have been infrequent and are generally controlled with reduction of dosage. A case of an extensive fixed drug eruption also has been reported.

Although rare, leukopenia and hepatic dysfunction including jaundice have been reported during therapy. Periodic blood counts and liver-function tests are advisable.

Ataxia with oxazepam has been reported in rare instances and does not appear to be specifically related to dose or age.

Although the following side reactions have not as yet been reported with oxazepam, they have occurred with related compounds (chlordiazepoxide and diazepam): paradoxical excitation with severe rage reactions, hallucinations, menstrual irregularities, change in EEG pattern, blood dyscrasias including agranulocytosis, blurred vision, diplopia, incontinence, stupor, disorientation, fever, and euphoria.

Transient amnesia or memory impairment has been reported in association with the use of benzodiazepines.

DRUG ABUSE AND DEPENDENCE

Oxazepam Capsules are classified by the Drug Enforcement Administration as a schedule IV controlled substance.

Withdrawal symptoms, similar in character to those noted with barbiturates and alcohol (convulsions, tremor, abdominal and muscle cramps, vomiting, and sweating), have occurred following abrupt discontinuance of oxazepam. The more severe withdrawal symptoms have usually been limited to those patients who received excessive doses over an extended period of time. Generally milder withdrawal symptoms (e.g., dysphoria and insomnia) have been reported following abrupt discontinuance of benzodiazepines taken continuously at therapeutic levels for several months. Consequently, after extended therapy, abrupt discontinuation should generally be avoided and a gradual dosage-tapering schedule followed. Addiction-prone individuals (such as drug addicts or alcoholics) should be under careful surveillance when receiving oxazepam or other psychotropic agents because of the predisposition of such patients to habituation and dependence.

OVERDOSAGE

In the management of overdosage with any drug, it should be borne in mind that multiple agents may have been taken.

Symptoms:

Overdosage of benzodiazepines is usually manifested by varying degrees of central nervous system depression ranging from drowsiness to coma. In mild cases, symptoms include drowsiness, mental confusion and lethargy. In more serious cases, and especially when other drugs or alcohol were ingested, symptoms may include ataxia, hypotonia, hypotension, hypnotic state, stage one (1) to three (3) coma, and very rarely, death.

Management:

Induced vomiting and/or gastric lavage should be undertaken, followed by general supportive care, monitoring of vital signs, and close observation of the patient. Hypotension, though unlikely, usually may be controlled with norepinephrine bitartrate injection. The value of dialysis has not been adequately determined for oxazepam.

The benzodiazepine antagonist flumazenil may be used in hospitalized patients as an adjunct to, not as a substitute for, proper management of benzodiazepine overdose. The prescriber should be aware of a risk of seizure in association with flumazenil treatment, particularly in long-term benzodiazepine users and in cyclic antidepressant overdose. The complete flumazenil package insert including CONTRAINDICATIONS, WARNINGS, and PRECAUTIONS should be consulted prior to use.

DOSAGE AND ADMINISTRATION

Because of the flexibility of this product and the range of emotional disturbances responsive to it, dosage should be individualized for maximum beneficial effects.

USUAL DOSE

Mild-to-moderate anxiety, with associated tension, irritability, agitation, or related symptoms of functional origin or secondary to organic disease. | 10 to 15 mg, 3 or 4 times daily
Severe anxiety syndromes, agitation, or anxiety associated with depression. | 15 to 30 mg, 3 or 4 times daily
Older patients with anxiety, tension, irritability, and agitation. | Initial dosage: 10 mg, 3 times daily. If necessary, increase cautiously to 15 mg, 3 or 4 times daily.
Alcoholics with acute inebriation, tremulousness, or anxiety on withdrawal. | 15 to 30 mg, 3 or 4 times daily

This product is not indicated in pediatric patients under 6 years of age. Absolute dosage for pediatric patients 6 to 12 years of age is not established.

HOW SUPPLIED

Repackaged by Aphena Pharma Solutions - TN.
See Repackaging Information for available configurations.

Oxazepam capsules are available as follows:

10 mg — Each pink opaque gelatin #4 capsule printed with and 067 in black ink on both cap and body contains 10 mg of Oxazepam, USP. Capsules are supplied in bottles of 100 (NDC 0228-2067-10) and 500 (NDC 0228-2067-50).

15 mg — Each red opaque gelatin #4 capsule printed with and 069 in black ink on both cap and body contains 15 mg of Oxazepam, USP. Capsules are supplied in bottles of 100 (NDC 0228-2069-10) and 500 (NDC 0228-2069-50).

30 mg — Each maroon opaque gelatin #4 capsule printed with and 073 in blue ink on both cap and body contains 30 mg of Oxazepam, USP. Capsules are supplied in bottles of 100 (NDC 0228-2073-10).

Keep tightly closed.

Dispense in a tight, light-resistant container as defined in the USP.

Store at 25(C (77(F); excursions permitted to 15(to 30(C (59(to 86(F).

ANIMAL PHARMACOLOGY AND/OR ANIMAL TOXICOLOGY

In mice, oxazepam exerts an anticonvulsant (anti-Metrazol®) activity at 50-percent-effective doses of about 0.6 mg/kg orally. (Such anticonvulsant activity of benzodiazepines correlates with their tranquilizing properties.) To produce ataxia (rotabar test) and sedation (abolition of spontaneous motor activity), the 50-percent-effective doses of this product are greater than 5 mg/kg orally. Thus, about ten times the therapeutic (anticonvulsant) dose must be given before ataxia ensues, indicating a wide separation of effective doses and doses inducing side effects.

In evaluation of antianxiety of compounds, conflict behavioral tests in rats differentiate continuous response for food in the presence of anxiety-provoking stress (shock) from drug-induced motor incoordination. This product shows significant separation of doses required to relieve anxiety and doses producing sedation or ataxia. Ataxia-producing doses exceed those of related CNS-acting drugs.

Acute oral LD50 in mice is greater than 5000 mg/kg, compared to 800 mg/kg for a related compound (chlordiazepoxide).

Subacute toxicity studies in dogs for four weeks at 480 mg/kg daily showed no specific changes; at 960 mg/kg two out of eight died with evidence of circulatory collapse. This wide margin of safety is significant compared to chlordiazepoxide HCl, which showed nonspecific changes in six dogs at 80 mg/kg. On chlordiazepoxide, two out of six died with evidence of circulatory collapse at 127 mg/kg, and six out of six died at 200 mg/kg daily. Chronic toxicity studies of oxazepam in dogs at 120 mg/kg/day for 52 weeks produced no toxic manifestation.

Fatty metamorphosis of the liver has been noted in six-week toxicity studies in rats given this product at 0.5% of the diet. Such accumulations of fat are considered reversible, as there is no liver necrosis or fibrosis.

Breeding studies in rats through two successive litters did not produce fetal abnormality.

Oxazepam has not been adequately evaluated for mutagenic activity.

In a carcinogenicity study, oxazepam was administered with diet to rats for two years. Male rats receiving 30 times the maximum human dose showed a statistical increase, when compared to controls, in benign thyroid follicular cell tumors, testicular interstitial cell adenomas, and prostatic adenomas. An earlier published study reported that mice fed dietary dosages of 35 or 100 times the human daily dose of oxazepam for 9 months developed a dose-related increase in liver adenomas.^1 In an independent analysis of some of the microscopic slides from this mouse study, several of these tumors were classified as liver carcinomas. At this time, there is no evidence that clinical use of oxazepam is associated with tumors.

REFERENCES

1. FOX, K.A, LAHCEN, R.B.: Liver-cell Adenomas and Peliosis Hepatis in Mice Associated with Oxazepam. Res. Commun. Chem. Pathol. Pharmacol. 8:481-488, 1974.

Manufactured by:

Actavis Elizabeth LLC

200 Elmora Avenue, Elizabeth, NJ 07207 USA

40-9188

Revised — March 2012

Repackaging Information

Please reference the How Supplied section listed above for a description of individual tablets or capsules. This drug product has been received by Aphena Pharma - TN in a manufacturer or distributor packaged configuration and repackaged in full compliance with all applicable cGMP regulations. The package configurations available from Aphena are listed below:

Count | 10mg | 15mg
30 | 67544-117-30 | 67544-268-30
60 | 67544-117-53 | 67544-268-53
90 | 67544-117-60 | 67544-268-60
120 | 67544-117-70 | 67544-268-70

Store between 20°-25°C (68°-77°F). See USP Controlled Room Temperature. Dispense in a tight light-resistant container as defined by USP. Keep this and all drugs out of the reach of children.

Repackaged by:
Cookeville, TN 38506
20140331SC

PRINCIPAL DISPLAY PANEL - 10mg

NDC 67544-117 - Oxazepam 10mg - Rx Only

PRINCIPAL DISPLAY PANEL - 15mg

NDC 67544-268 - Oxazepam 15mg - Rx Only